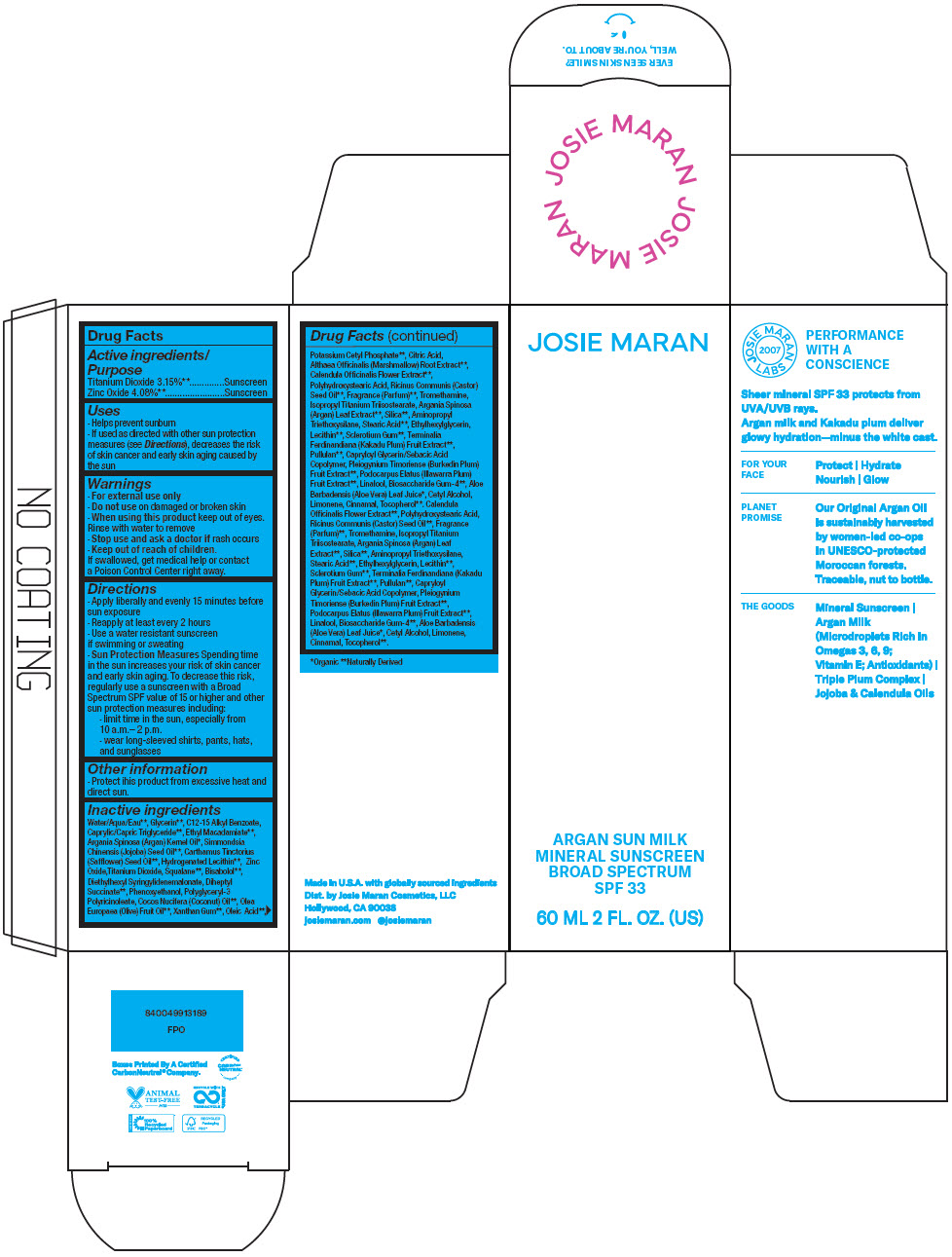 DRUG LABEL: JOSIE MARAN ARGAN SUN MILK MINERAL SUNSCREEN BROAD SPECTRUM SPF 33
NDC: 66163-4550 | Form: LIQUID
Manufacturer: Cosmetic Solutions LLC
Category: otc | Type: HUMAN OTC DRUG LABEL
Date: 20260130

ACTIVE INGREDIENTS: Titanium Dioxide 3.15 g/100 mL; Zinc Oxide 4.08 g/100 mL
INACTIVE INGREDIENTS: Water

JOSIE MARAN ARGAN SUN MILK MINERAL SUNSCREEN BROAD SPECTRUM SPF 33

Drug Facts

ACTIVE INGREDIENT

Active ingredients | Purpose
Titanium Dioxide 3.15% [Naturally Derived] | Sunscreen
Zinc Oxide 4.08% | Sunscreen

Uses

- Helps prevent sunburn
- If used as directed with other sun protection measures (see Directions), decreases the risk of skin cancer and early skin aging caused by the sun

Warnings

- For external use only

- Do not use on damaged or broken skin

- When using this product keep out of eyes. Rinse with water to remove

- Stop use and ask a doctor if rash occurs

- Keep out of reach of children.

If swallowed, get medical help or contact a Poison Control Center right away.

Directions

- Apply liberally and evenly 15 minutes before sun exposure
- Reapply at least every 2 hours
- Use a water resistant sunscreen if swimming or sweating
- Sun Protection Measures Spending time in the sun increases your risk of skin cancer and early skin aging. To decrease this risk, regularly use a sunscreen with a Broad Spectrum SPF value of 15 or higher and other sun protection measures including:
  - limit time in the sun, especially from 10 a.m.– 2 p.m.
  - wear long-sleeved shirts, pants, hats, and sunglasses

Other information

- Protect ihis product from excessive heat and direct sun.

Inactive ingredients

Water/Aqua/Eau [Naturally Derived] , Glycerin, C12-15 Alkyl Benzoate, Caprylic/Capric Triglyceride, Ethyl Macadamiate, Argania Spinosa (Argan) Kernel Oil [Organic] , Simmondsia Chinensis (Jojoba) Seed Oil, Carthamus Tinctorius (Safflower) Seed Oil, Hydrogenated Lecithin, Zinc Oxide,Titanium Dioxide, Squalane, Bisabolol, Diethylhexyl Syringylidenemalonate, Diheptyl Succinate, Phenoxyethanol, Polyglyceryl-3 Polyricinoleate, Cocos Nucifera (Coconut) Oil, Olea Europaea (Olive) Fruit Oil, Xanthan Gum, Oleic Acid, Potassium Cetyl Phosphate, Citric Acid, Althaea Officinalis (Marshmallow) Root Extract, Calendula Officinalis Flower Extract, Polyhydroxystearic Acid, Ricinus Communis (Castor) Seed Oil, Fragrance (Parfum), Tromethamine, Isopropyl Titanium Triisostearate, Argania Spinosa (Argan) Leaf Extract, Silica, Aminopropyl Triethoxysilane, Stearic Acid, Ethylhexylglycerin, Lecithin, Sclerotium Gum, Terminalia Ferdinandiana (Kakadu Plum) Fruit Extract, Pullulan, Capryloyl Glycerin/Sebacic Acid Copolymer, Pleiogynium Timoriense (Burkedin Plum) Fruit Extract, Podocarpus Elatus (Illawarra Plum) Fruit Extract, Linalool, Biosaccharide Gum-4, Aloe Barbadensis (Aloe Vera) Leaf Juice, Cetyl Alcohol, Limonene, Cinnamal, Tocopherol. Calendula Officinalis Flower Extract, Polyhydroxystearic Acid, Ricinus Communis (Castor) Seed Oil, Fragrance (Parfum), Tromethamine, Isopropyl Titanium Triisostearate, Argania Spinosa (Argan) Leaf Extract, Silica, Aminopropyl Triethoxysilane, Stearic Acid, Ethylhexylglycerin, Lecithin, Sclerotium Gum, Terminalia Ferdinandiana (Kakadu Plum) Fruit Extract, Pullulan, Capryloyl Glycerin/Sebacic Acid Copolymer, Pleiogynium Timoriense (Burkedin Plum) Fruit Extract, Podocarpus Elatus (Illawarra Plum) Fruit Extract, Linalool, Biosaccharide Gum-4, Aloe Barbadensis (Aloe Vera) Leaf Juice, Cetyl Alcohol, Limonene, Cinnamal, Tocopherol.

Dist. by Josie Maran Cosmetics, LLC
Hollywood, CA 90038

PRINCIPAL DISPLAY PANEL - 60 mL Bottle Carton

JOSIE MARAN

ARGAN SUN MILK
MINERAL SUNSCREEN
BROAD SPECTRUM
SPF 33
60 ML 2 FL. OZ. (US)